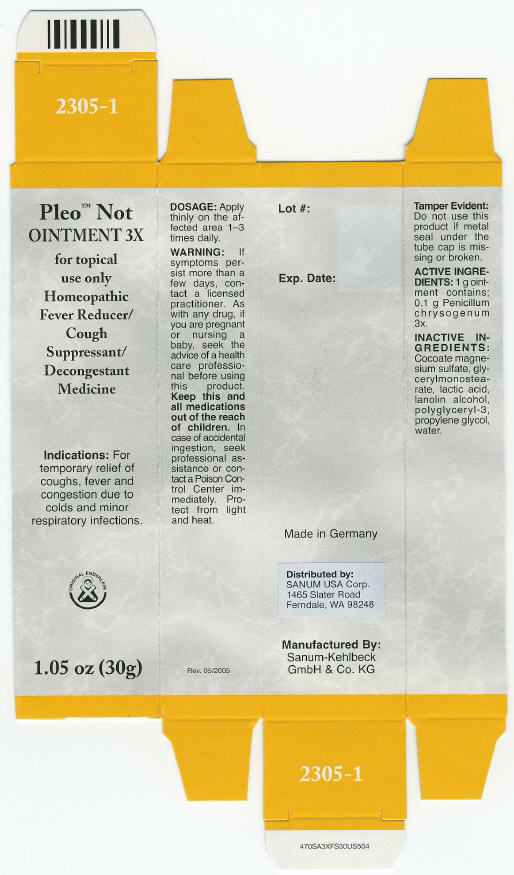 DRUG LABEL: Pleo Not
NDC: 60681-2305 | Form: OINTMENT
Manufacturer: Sanum Kehlbeck GmbH & Co. KG
Category: homeopathic | Type: HUMAN OTC DRUG LABEL
Date: 20091014

ACTIVE INGREDIENTS: penicillium chrysogenum var. chrysogenum 3 [HP_X]/30 g
INACTIVE INGREDIENTS: glyceryl monostearate; lactic acid; propylene glycol; water

Pleo™ Not
OINTMENT 3X

for topical use only
Homeopathic Fever Reducer/Cough Suppressant/Decongestant Medicine

1.05 oz (30g)

Indications

For temporary relief of coughs, fever and congestion due to colds and minor respiratory infections.

DOSAGE

Apply thinly on the affected area 1–3 times daily.

WARNING

If symptoms persist more than a few days, contact a licensed practitioner. As with any drug, if you are pregnant or nursing a baby, seek the advice of a health care professional before using this product.

KEEP OUT OF REACH OF CHILDREN

Keep this and all medications out of the reach of children. In case of accidental ingestion, seek professional assistance or contact a Poison Control Center immediately.

STORAGE AND HANDLING

Protect from light and heat.

Tamper Evident

Do not use this product if metal seal under the tube cap is missing or broken.

ACTIVE INGREDIENTS

1 g ointment contains; 0.1 g Penicillum chrysogenum 3x.

INACTIVE INGREDIENTS

Cocoate magnesium sulfate, glycerylmonostearate, lactic acid, lanolin alcohol, polyglyceryl-3, propylene glycol, water.

Made in Germany

Distributed by:
SANUM USA Corp.
1465 Slater Road
Ferndale, WA 98248

Manufactured By:
Sanum-Kehlbeck
GmbH & Co. KG

Rev. 05/2005

PRINCIPAL DISPLAY PANEL - 30 g Ointment Carton

Pleo™ Not
OINTMENT 3X

for topical
use only
Homeopathic
Fever Reducer/
Cough
Suppressant/
Decongestant
Medicine

Indications: For
temporary relief of
coughs, fever and
congestion due to
colds and minor
respiratory infections.

ORIGINAL ENDERLEIN

1.05 oz (30g)